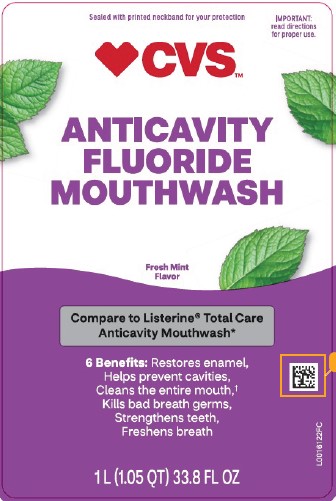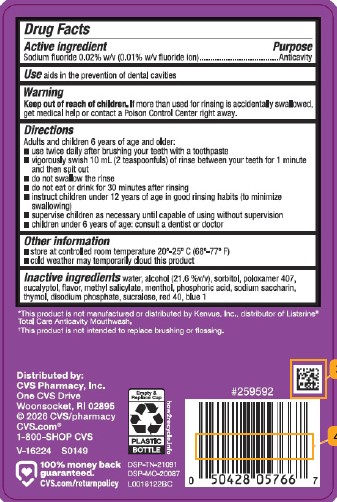 DRUG LABEL: Anticavity Fluoride Rinse
NDC: 59779-163 | Form: MOUTHWASH
Manufacturer: CVS Pharmacy, Inc.
Category: otc | Type: HUMAN OTC DRUG LABEL
Date: 20260211

ACTIVE INGREDIENTS: SODIUM FLUORIDE 0.1 mg/1 mL
INACTIVE INGREDIENTS: WATER; ALCOHOL; SORBITOL; POLOXAMER 407; EUCALYPTOL; METHYL SALICYLATE; MENTHOL; PHOSPHORIC ACID; SACCHARIN SODIUM; THYMOL; SODIUM PHOSPHATE, DIBASIC, ANHYDROUS; SUCRALOSE; FD&C RED NO. 40; FD&C BLUE NO. 1

CVS 163.005/163AF-AG
Anticavity Fluoride Rinse

Active Ingredient

Sodium fluoride 0.02% w/v (0.01% w/v fluoride ion)

Purpose

Anticavity

Use

aids in the prevention of dental cavities

Warnings

for this product

Keep out of reach of children.

If more than used for rinsing is accidentally swallowed, get medical help or contact a Poison Control Center right away.

Directions

Adults and children 6 years of age and older:

- use twice daily after brushing your teeth with a toothpaste
- vigorously swish 10 ml (2 teaspoonfuls) of rinse between your teeth for 1 minute and then spit out
- do not swallow the rinse
- do not eat or drink for 30 minutes after rinsing
- instruct children under 12 years of age in good rinsing habits (to minimize swallowing)
- supervise children as necessary until capable of using without supervision
- children under 6 years of age: consult a dentist or doctor

Other information

- store at controlled room temperature 20⁰ - 25⁰ C (68⁰ - 77⁰ F)
- cold weather may temporarily cloud this product

Inactive ingredients

water, alcohol (21.6 %v/v), sorbitol, poloxamer 407, eucalyptol, flavor, methyl salicylate, menthol, phosphoric acid, sodium saccharin, thymol, disodium phosphate, sucralose, red 40, blue 1

Disclaimers

*This product is not manufactured or distributed by Kenvue, Inc., distributor of Listerine® Total Care Anticavity Mouthwash.

†This product is not intended to replace brushing or flossing.

ADVERSE REACTION

Distributed by: CVS Pharmacy, Inc.

One CVS Drive, Woonsocket, RI 02895

©2026 CVS/pharmacy

CVS.com 1-800-SHOP CVS

100% Money Back Guaranteed.

CVS.com/returnpolicy

DSP-TN-21091

DSP-MO-20087

Empty & Replace Cap

PLASTIC BOTTLE

how2recycle.info

principal display panel

Sealed with printed neckband for your protection.

IMPORTANT: Read directions for proper use.

CVS™

Anticavity Fluoride Mouthwash

Fresh Mint Flavor

Compare to Listerine®Total Care Anticavity Mouthwash*

6 Benefits: Restores enamel,

Helps prevent cavities,

Cleans entire mouth,†

Kills bad breath germs,

Strengthens teeth,

Freshens breath

1 L (1.05 QT) 33.8 FL OZ